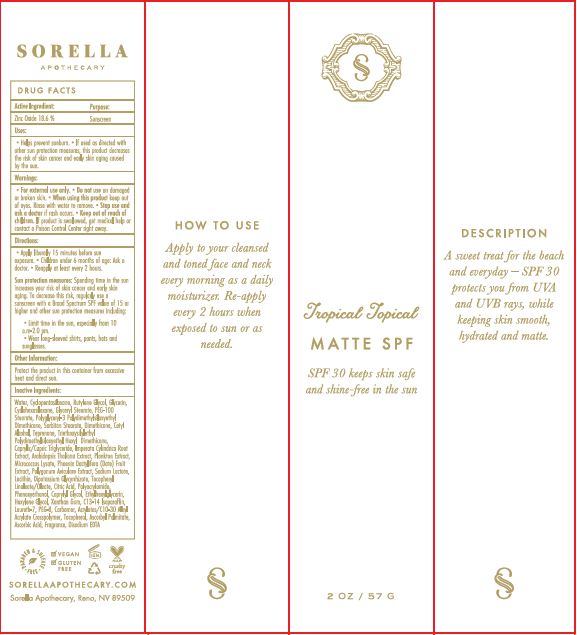 DRUG LABEL: Tropical Topical Matte SPF 30
NDC: 62742-4157 | Form: CREAM
Manufacturer: Allure Labs Inc
Category: otc | Type: HUMAN OTC DRUG LABEL
Date: 20171212

ACTIVE INGREDIENTS: ZINC OXIDE 186 mg/1 g
INACTIVE INGREDIENTS: WATER; DIMETHICONE CROSSPOLYMER (450000 MPA.S AT 12% IN CYCLOPENTASILOXANE); BUTYLENE GLYCOL; GLYCERIN; TRIEPOXYCYCLOHEXASILANE; GLYCERYL STEARATE SE; PEG-100 STEARATE; POLYGLYCERYL-3 POLYDIMETHYLSILOXYETHYL DIMETHICONE (4000 MPA.S); SORBITAN MONOSTEARATE; DIMETHICONE; CETYL ALCOHOL; TEPRENONE; CAPRYLIC/CAPRIC/LAURIC TRIGLYCERIDE; IMPERATA CYLINDRICA ROOT; ARABIDOPSIS THALIANA; MICROCOCCUS LUTEUS; PHOENIX DACTYLIFERA WHOLE; POLYGONUM AVICULARE WHOLE; SODIUM LACTATE; LECITHIN, SOYBEAN; TOCOPHEROL; CITRIC ACID ACETATE; POLYACRYLAMIDE (10000 MW); PHENOXYETHANOL; CAPRYLYL GLYCOL; ETHYLHEXYLGLYCERIN; HEXYLENE GLYCOL; XANTHAN GUM; C13-14 ISOPARAFFIN; LAURETH-7; PEG-8 DIMETHICONE; CARBOMER 934; (C10-C30)ALKYL METHACRYLATE ESTER; ASCORBYL PALMITATE; ASCORBIC ACID; EDETATE DISODIUM

Drug Facts

Active Ingredient:

Zinc Oxide - 18.6%

Purpose: Sunscreen

INDICATIONS AND USAGE

Use: Apply to your cleansed and toned face and neck every morning as a daily moisturizer. Re-apply every 2 hours when exposed to sun or as needed.

DOSAGE AND ADMINISTRATION

How to use: Apply to your cleansed and toned face and neck every morning as a daily moisturizer. Re-apply every 2 hours when exposed to sun or as needed.

INACTIVE INGREDIENT

Other Ingredients: Water, Cyclopentasiloxane, Butylene Glycol, Glycerin, Cyclohexasiloxane, Glyceryl Stearate, PEG-100 Stearate, Polyglyceryl-3 Polydimethylsiloxyethyl, Dimethicone, Sorbitan Stearate, Cetyl Alcohol, Teprenone, Triethoxysilylethyl Polydimethylsiloxyethyl Hexyl Dimethicone, Caprylic/Capric Triglyceride, Imperata Cylendrica Root Extract, Arabidopsis Thaliana Extract, Plankton Extract, Micrococcus Lysate, Phoenix Dactylifera (Date) Fruit Extract, Polygonum Aviculare Extract, Sodium Lactate, Lecithin, Dipotassium Glycyrrhizate, Tocopheryl Linoleate/ Oleate, Citric Acid, Polyacrylamide, Phenoxyethanol, Caprylyl Glycol, Ethylhexylglycerine, Hexylene Glycol, Xanthan Gum, C13-14 Isoparaffin, Laureth-7, PEG-8, Carbomer, Acrylates/C10-30 Alkyl Acrylate Crosspolymer, Tocopherol, Asccorbyl Palmitate, Ascorbc Acid, Fragrance, Disodium EDTA.

PACKAGE LABEL

SORELLAAPOTHECARY.COM

Sorella Apothecary, Reno, NV 89509.